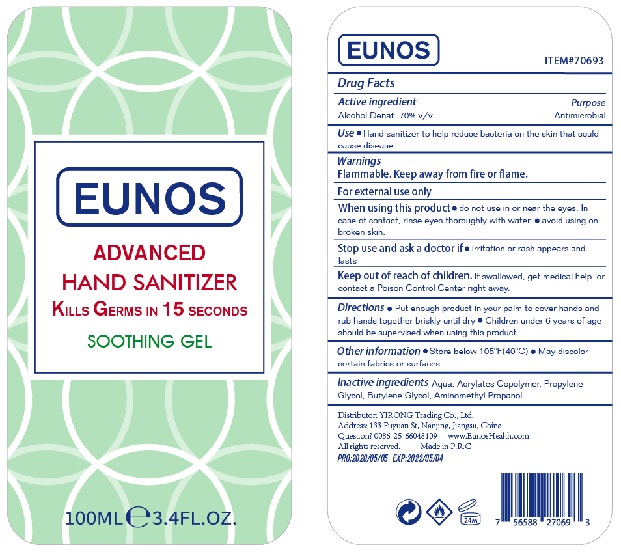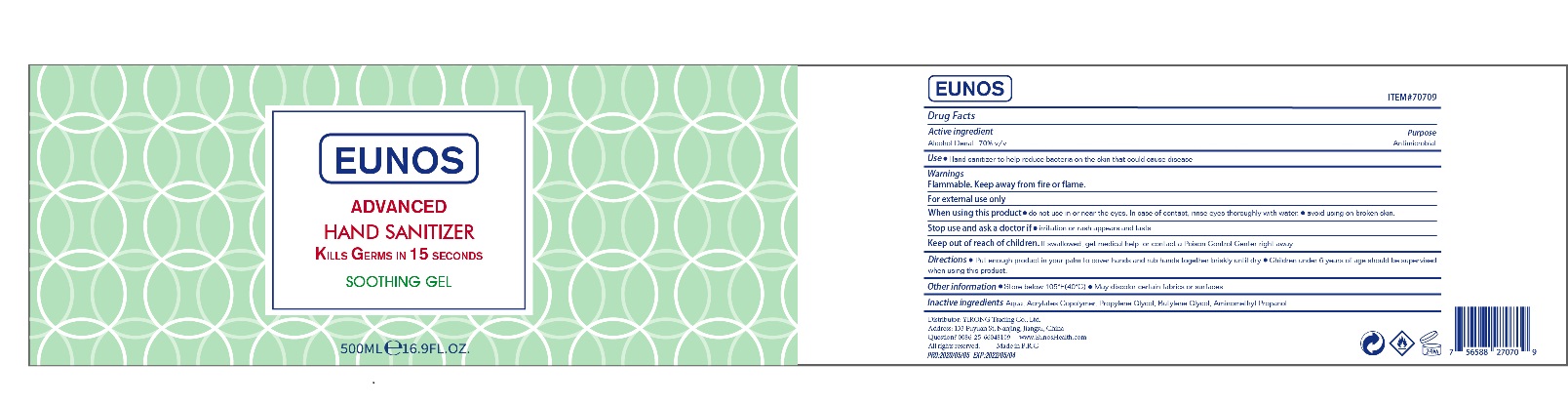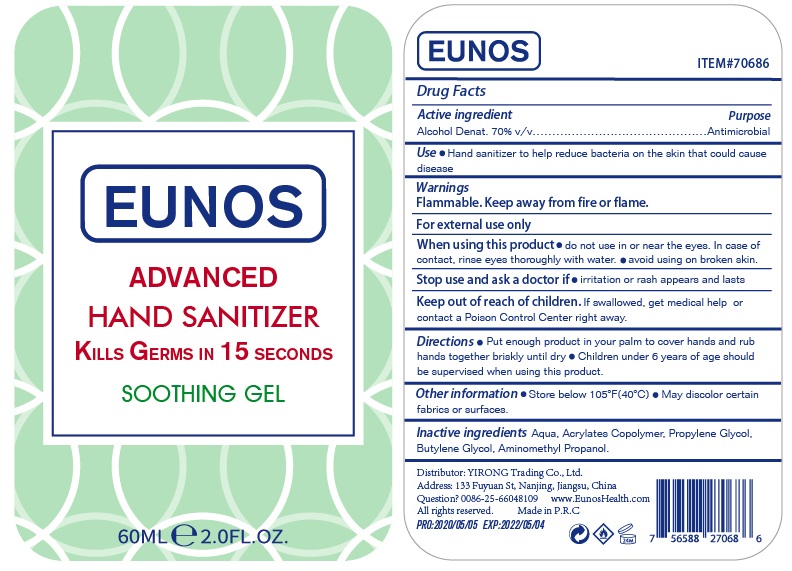 DRUG LABEL: EUNOS advanced hand sanitizer
NDC: 75007-001 | Form: GEL
Manufacturer: YIRONG TRADING (NANJING) CO., LTD
Category: otc | Type: HUMAN OTC DRUG LABEL
Date: 20200426

ACTIVE INGREDIENTS: ALCOHOL 70 mL/100 mL
INACTIVE INGREDIENTS: WATER; BUTYL ACRYLATE/METHYL METHACRYLATE/METHACRYLIC ACID COPOLYMER (18000 MW); PROPYLENE GLYCOL; BUTYLENE GLYCOL; AMINOMETHYLPROPANOL

Active Ingredient

Alcohol Denat.70% v/v.

Purpose

Antimicrobial

Uses

Hand sanitizer to help reduce bacteria on the skin that could cause disease.

Warnings

Flammable. Keep away from fire or flame.

For external use only

When using this product

- do not use in or near the eyes. In case of contact, rinse eyes thoroughly with water.
- avoid using on broken skin.

Stop use and ask a doctor if irritation or rash appears and lasts

Keep out of reach of children. If swallowed, get medical help or contact a Poison Control Center right away.

Directions

- Put enough product in your palm to cover hands and rub hands together briskly until dry.
- Children under 6 years of age should be supervised when using this product

Other Information

- Store below 105℉(40℃).
- May discolor certain fabrics or surfaces.

Inactive ingredients

Aqua, Acrylates Copolymer, Propylene Glycol, Butylene Clycol, Aminomethyl Propanol

Package Label - Principal Display Panel

60 mL Label

100 mL Label

500 mL Label